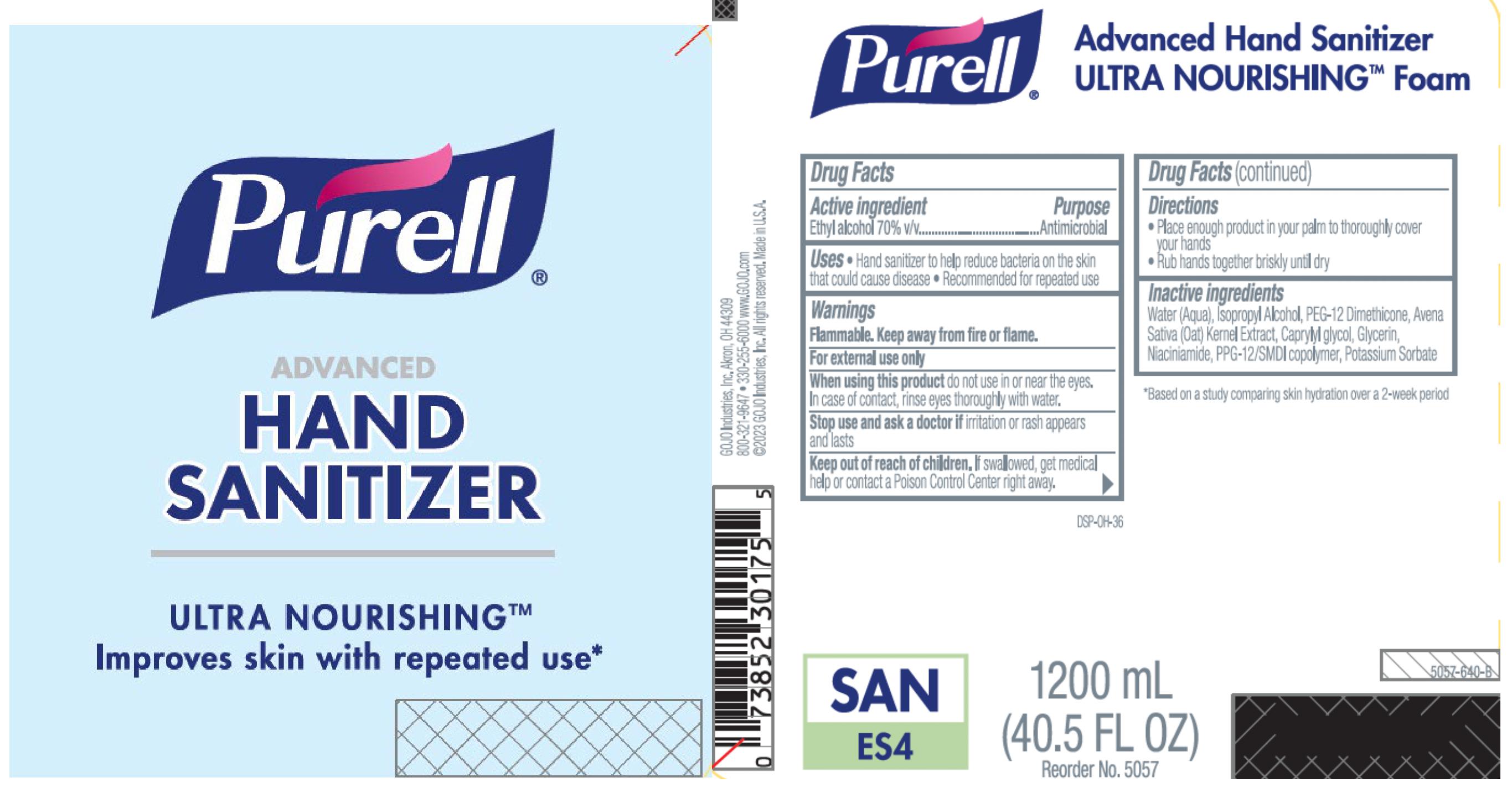 DRUG LABEL: PURELL Advanced Hand Sanitizer ULTRA NOURISHING Foam
NDC: 21749-856 | Form: LIQUID
Manufacturer: GOJO Industries, Inc.
Category: otc | Type: HUMAN OTC DRUG LABEL
Date: 20241216

ACTIVE INGREDIENTS: ALCOHOL 70 mL/100 mL
INACTIVE INGREDIENTS: WATER; ISOPROPYL ALCOHOL; PEG-12 DIMETHICONE (300 CST); OAT; CAPRYLYL GLYCOL; GLYCERIN; NIACINAMIDE; PPG-12/SMDI COPOLYMER; POTASSIUM SORBATE

PURELL Advanced Hand Sanitizer ULTRA NOURISHING Foam

Active ingredient

Ethyl Alcohol 70% v/v

Purpose

Antimicrobial

Uses

• Hand sanitizer to help reduce bacteria on the skin that could cause disease

• Recommended for repeated use

Warnings

Flammable. Keep away from fire or flame.

For external use only.

WHEN USING

When using this productdo not use in or near the eyes. In case of contact, rinse eyes thoroughly with water.

Stop use and ask a doctor ifirritation or rash appears and lasts.

Keep out of reach of children.If swallowed, get medical help or contact a Poison Control Center right away.

Directions

• Place enough product in your palm to thoroughly cover your hands

• Rub hands together briskly until dry

Inactive ingredients

Water (Aqua), Isopropyl Alcohol, PEG-12 Dimethicone, Avena Sativa (Oat) Kernel Extract, Caprylyl glycol, Glycerin, Niaciniamide, PPG-12/SMDI copolymer, Potassium Sorbate